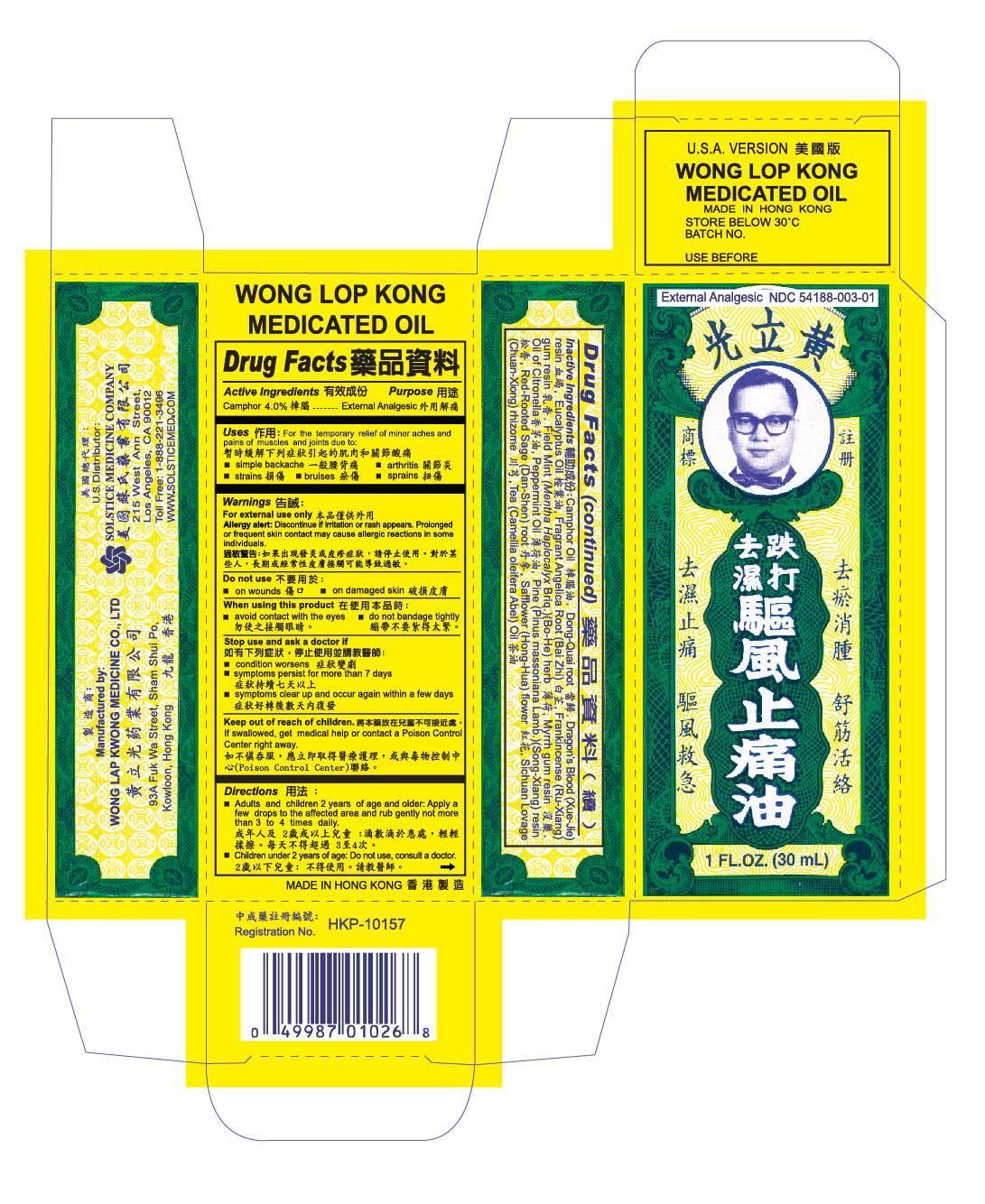 DRUG LABEL: WONG LOP KONG MEDICATED
NDC: 54188-003 | Form: OIL
Manufacturer: WONG LAP KWONG MEDICINE COMPANY LIMITED
Category: otc | Type: HUMAN OTC DRUG LABEL
Date: 20191113

ACTIVE INGREDIENTS: CAMPHOR (SYNTHETIC) 4 g/100 mL
INACTIVE INGREDIENTS: CAMPHOR OIL; ANGELICA SINENSIS ROOT; DRAGON'S BLOOD; EUCALYPTUS OIL; ANGELICA DAHURICA ROOT; FRANKINCENSE; MENTHA ARVENSIS WHOLE; MYRRH; CITRONELLA OIL; PEPPERMINT OIL; PINUS MASSONIANA RESIN; SALVIA OFFICINALIS ROOT; SAFFLOWER; LIGUSTICUM SINENSE SUBSP. CHUANXIONG WHOLE; CAMELLIA OLEIFERA WHOLE

DRUG FACTS

Active ingredients
Camphor 4%

Purpose
External analgesic

Uses
For the temporary relief of minor aches and pains of muscles and joints due to:
simple backache, arthritis, strains, bruises, sprai

Warnings
For external use only
Allergy alert: Discontinue if irritation or rash appears. Prolonged or frequent skin contact may cause allergic reactions in some individuals.

Do not use
on wounds, on damaged skin

When using this product
avoid contact with the eyes
do not bandage tightly

Stop use and ask a doctor if
condition worsens
symptoms persist for more than 7 days
symptoms clear up and occur again within a few days

Keep out of reach of children to avoid accidental poisoning.
If swallowed, get medical help or contact a Poison Control Center right away.

Directions
Adults and children 2 years of age and older: Apply a few drops to the affected area and rub gently not more than 3 to 4 times daily.
Children under 2 years of age: Do not use, consult a doctor.

Other information
keep container tightly closed
store at 15E to 30 C (59 to 86 F)

Inactive ingredients
Camphor Oil, Dong-Quai root, Dragon’s Blood resin, Eucalyptus Oil, Fragrant Angelica Root, Frankincense gum resin, Field Mint herb, Myrrh gum resin, Oil of Citronella, Peppermint Oil, Pine resin, Red-Rooted Sage root, Safflower flower, Sichuan Lovage rhizome, Tea Oil

Questions or comments? (888) 221-3496 M-F 9 am to 5 pm

PACKAGE LABEL

WONG LOP KONG MEDICATED OIL, External Analgesic, NDC 54188–003-01, 1 fl oz (30 mL)